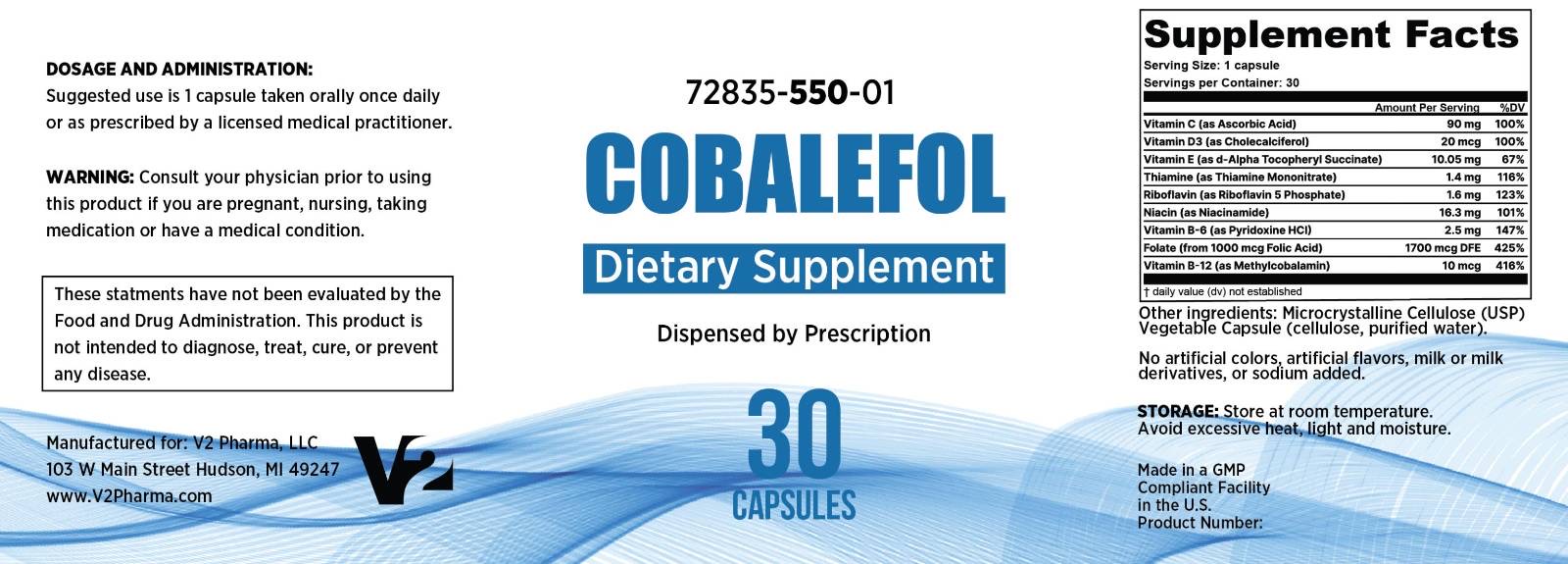 DRUG LABEL: Cobalefol
NDC: 72835-550 | Form: CAPSULE
Manufacturer: V2 Pharma LLC
Category: prescription | Type: HUMAN PRESCRIPTION DRUG LABEL
Date: 20250516

ACTIVE INGREDIENTS: ASCORBIC ACID 90 mg/1 1; CHOLECALCIFEROL 20 ug/1 1; .ALPHA.-TOCOPHEROL SUCCINATE, D- 10.5 mg/1 1; THIAMINE MONONITRATE 1.4 mg/1 1; RIBOFLAVIN 5'-PHOSPHATE 1.6 mg/1 1; NIACINAMIDE 16.3 mg/1 1; PYRIDOXINE HCL 2.5 mg/1 1; FOLIC ACID 1700 ug/1 1; METHYLCOBALAMIN 10 ug/1 1
INACTIVE INGREDIENTS: MICROCRYSTALLINE CELLULOSE; HYPROMELLOSE, UNSPECIFIED

Cobalefol

Supplement Facts

Cobalefol Capsules - Vitamins dispensed by prescription

Supplement Facts

Serving Size: 1 Capsule

Servings Per Bottle: 30

Ingredients | Amount Per Serving | %DV
Vitamin C (as Ascorbic Acid) | 90 mg | 100%
Vitamin D3 (as Cholecalciferol) | 20 mcg | 100%
Vitamin E (as d-Alpha Tocopheryl Succinate) | 10.05 mg | 67%
Thiamine (as Thiamine Mononitrate) | 1.4 mg | 116%
Riboflavin (as Riboflavin 5 Phosphate) | 1.6 mg | 123%
Niacin (as Niacinamide) | 16.3 mg | 101%
Vitamin B-6 (as Pyridoxine HCl) | 2.5 mg | 147%
Folate (from 1000 mcg Folic Acid) | 1700 mcg DFE | 425%
Vitamin B-12 (as Methylcobalamin) | 10 mcg | 416%

Other ingredients: Microcrystalline Cellulose (USP), Vegetable Capsule (cellulose, purified water)

Description:

Cobalefol is an orally administered vitamin formulation for the clinical dietary management of suboptimal nutritional status in patients where advanced folate supplementation is needed. Cobalefol provides significant amounts of Vitamins B6, B12, C, D3, E, riboflavin, niacinamide, and thiamine mononitrate to supplement the diet.

Contraindications

Cobalefol is contraindicated in patients with a known hypersensitivity to any of the contained ingredients. Do not take this product if you are presently taking mineral oil, unless directed by a licensed medical practitioner.

Precaution

Folic acid alone is improper therapy in the treatment of pernicious anemia and other megaloblastic anemias where vitamin B is deficient. Folic acid in doses above 1 mg daily may obscure pernicious anemia in that hematologic remission can occur while neurological manifestations progress. Cobalefol should only be used under the direction and supervision of a licensed medical practitioner.

WARNINGS

KEEP COBALEFOL OUT OF THE REACH OF CHILDREN.
In case of accidental overdose, call a licensed medical practitioner or poison control center immediately.
For use under the supervision of a licensed medical practitioner.

Consult your physician prior to using Cobalefol if you are pregnant, nursing, taking medication, or have a medical condition.

Doseage and Administration

Suggested use is 1 capsule taken orally once daily or as prescribed by a licensed medical practitioner.

Storage and Handling

Store at room temperature. Avoid excessive heat, light, and moisture.

Statements

These statements have not been evaluated by the Food and Drug Administration. This product is not intended to diagnose, treat, cure, or prevent any disease.

How Supplied

Cobalefol vitamin capsules are available in 30 count bottles. 72835-550-01

Manufactured for:
V2 Pharma, LLC
103 W Main Street
Hudson, MI 49247